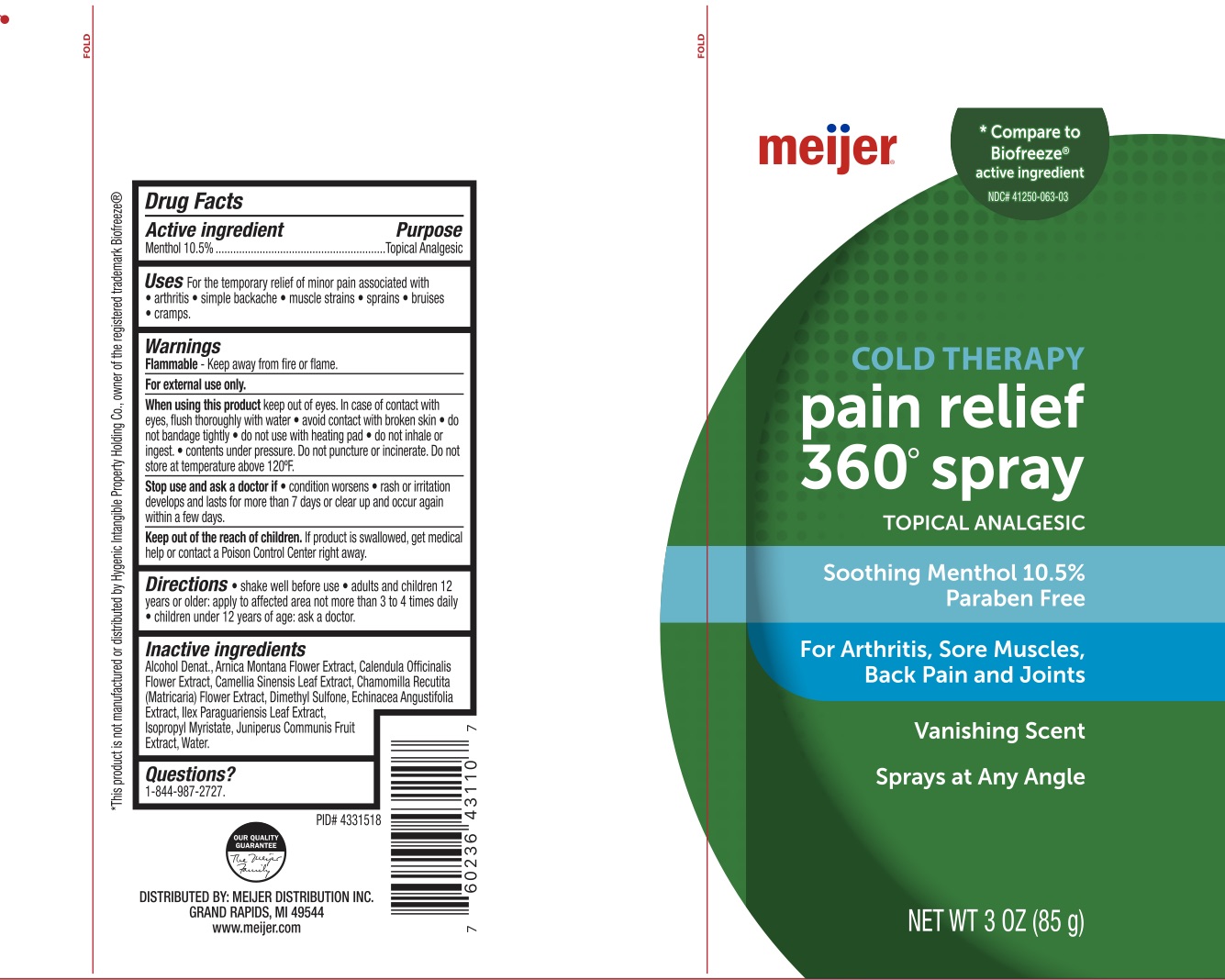 DRUG LABEL: Meijer Pain Relief
NDC: 79481-0639 | Form: SPRAY
Manufacturer: Meijer
Category: otc | Type: HUMAN OTC DRUG LABEL
Date: 20241220

ACTIVE INGREDIENTS: MENTHOL 10.5 g/100 g
INACTIVE INGREDIENTS: WATER; ARNICA MONTANA FLOWER; ALCOHOL; CALENDULA OFFICINALIS FLOWER; CHAMOMILE; ILEX PARAGUARIENSIS LEAF; ISOPROPYL MYRISTATE; JUNIPER BERRY; ECHINACEA ANGUSTIFOLIA; GREEN TEA LEAF; DIMETHYL SULFONE

Meijer Pain Relief Spray, Menthol 10.5%

ACTIVE INGREDIENT

Menthol 10.5%

PURPOSE

Topical Analgesic

INDICATIONS AND USAGE

For the temporary relief of minor pain associated with arthritis, simple backache, muscle strains, sprains, and bruises.

WARNINGS

For external use only. Flammable--Keep away from fire or flame. When using this product avoid contact with eyes. In case of contact with eyes, flush thoroughly with water, do not apply to wounds or damaged skin, and do not bandage tightly, do not use with a heating pad. Contents under pressure. Do not puncture or incinerate. Do not store at temperature above 120F. . Stop use and ask a doctor if condition worsens, if symptoms persist for more than 7 days or clear up and occur again within a few days.

KEEP OUT OF REACH OF CHILDREN

If swallowed, get medical help or contact a Poison Control Center right away.

DOSAGE AND ADMINISTRATION

Shake well before use. Adults and children 12 years of age and older, apply to the affected area not more than 3 to 4 times daily. Children under 12 years of age: ask a doctor.

INACTIVE INGREDIENT

Alcohol Denat., Arnica Montana Flower Extract, Calendula Officinalis Flower Extract, Camellia Sinensis Leaf Extract, Chamomilla Recutita (Matricaria) Flower Extract, Dimethyl Sulfone, Echinacea Angustifolia Extract, Ilex Paraguariensis Leaf Extract, Isopropyl Myristate, Juniperus Communis Fruit Extract, Water